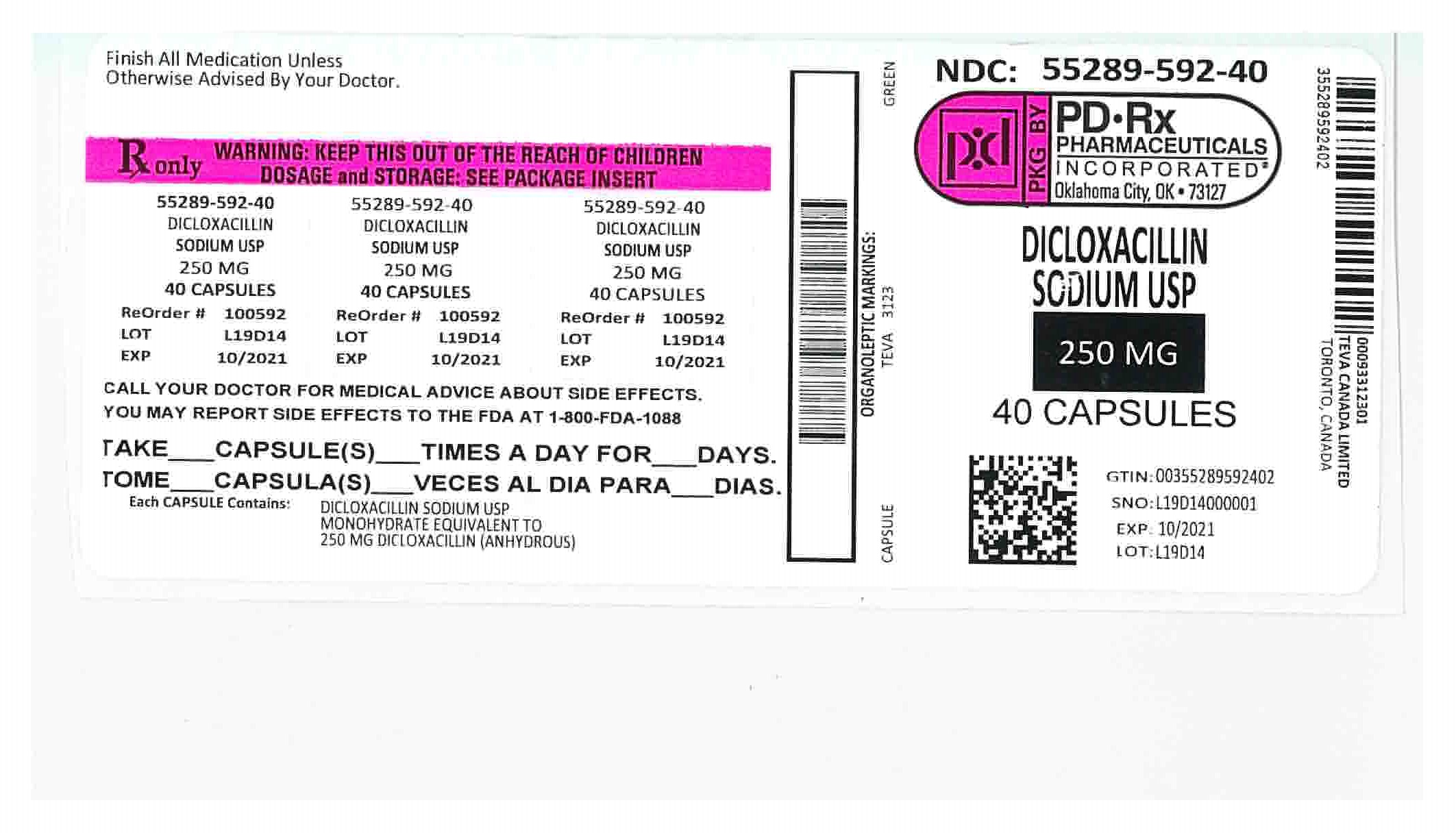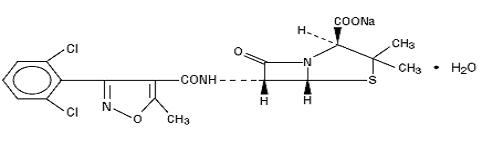 DRUG LABEL: Dicloxacillin Sodium
NDC: 55289-592 | Form: CAPSULE
Manufacturer: PD-Rx Pharmaceuticals, Inc.
Category: prescription | Type: HUMAN PRESCRIPTION DRUG LABEL
Date: 20251020

ACTIVE INGREDIENTS: DICLOXACILLIN SODIUM 250 mg/1 1
INACTIVE INGREDIENTS: MAGNESIUM STEARATE; FD&C BLUE NO. 2--ALUMINUM LAKE; FD&C RED NO. 40; D&C YELLOW NO. 10; GELATIN; SHELLAC; SODIUM LAURYL SULFATE; SORBITAN MONOLAURATE; FERROSOFERRIC OXIDE; TITANIUM DIOXIDE; PROPYLENE GLYCOL; D&C YELLOW NO. 10 ALUMINUM LAKE; FD&C BLUE NO. 1 ALUMINUM LAKE; FD&C BLUE NO. 1

Dicloxacillin Sodium Capsules USP
Rx only

To reduce the development of drug resistant bacteria and maintain the effectiveness of dicloxacillin sodium capsules and other antibacterial drugs, dicloxacillin sodium capsules should be used only to treat or prevent infections that are proven or strongly suspected to be caused by bacteria.

DESCRIPTION

Dicloxacillin sodium, USP is an antibacterial agent of the isoxazolyl penicillin series. It is a penicillinase resistant, acid resistant semisynthetic penicillin suitable for oral administration.

It is monosodium (2 S,5 R,6 R)-6-[3-(2,6-dichlorophenyl)-5-methyl-4-isoxazolecarboxamido]-3,3-dimethyl-7-oxo-4-thia-1-azabicyclo [3.2.0]heptane-2-carboxylate monohydrate, and has following structural formula:

C19H16Cl2N3NaO5 S·H2O MW 510.32

Each capsule for oral administration contains dicloxacillin sodium, USP equivalent to 250 mg or 500 mg of dicloxacillin. The inactive ingredient is Magnesium Stearate. The capsule shells and print constituents contains D&C Yellow #10 Aluminum Lake, FD&C Blue #1 Aluminum Lake, FD&C Blue #1, FD&C Blue #2 Aluminum Lake, FD&C Red #40 Aluminum Lake, D&C Yellow #10, Gelatin, Shellac, Sodium Lauryl Sulfate, Sorbitan Monolaurate, Black Iron Oxide, Titanium Dioxide, Propylene Glycol.

CLINICAL PHARMACOLOGY

Microbiology

Mechanism of Action

Penicillinase-resistant penicillins exert a bactericidal action against penicillin-susceptible microorganisms during the state of active multiplication. All penicillins inhibit the biosynthesis of the bacterial cell wall.

Antibacterial Activity

Dicloxacillin sodium has been shown to be active against most isolates of the following microorganisms, both in vitro and in clinical infections as described in the INDICATIONS AND USAGE section.

Gram-positive Bacteria

Staphylococcus spp.

Susceptibility Testing

For specific information regarding susceptibility test interpretive criteria and associated test methods and quality control standards recognized by FDA for this drug, please see: https://www.fda.gov/STIC.

Pharmacokinetics

Dicloxacillin sodium is resistant to destruction by acid.

Absorption of dicloxacillin sodium after oral administration is rapid but incomplete; peak blood levels are achieved in 1 to 1.5 hours. In one study, after ingestion of a single 500 mg oral dose, peak serum concentrations range from 10 to 17 mcg/mL for dicloxacillin.

Oral absorption of dicloxacillin is delayed when the drugs are administered after meals.

Once absorbed, dicloxacillin sodium is 97.9 ± 0.6 percent bound to serum protein, mainly albumin. Dicloxacillin sodium vary in the extent to which they are distributed in the body fluids. With normal doses, insignificant concentrations are found in the cerebrospinal fluid and aqueous humor. Dicloxacillin sodium is found in therapeutic concentrations in the pleural, bile and amniotic fluids.

Dicloxacillin sodiumis rapidly excreted, primarily as unchanged drug in the urine by glomerular filtration and active tubular secretion. The elimination half-life for dicloxacillin is about 0.7 hour. Nonrenal elimination includes hepatic inactivation and excretion in bile.

Dicloxacillin is not dialyzable. Only minimal amounts are removed by hemodialysis or peritoneal dialysis.

INDICATIONS AND USAGE

To reduce the development of drug-resistant bacteria and maintain the effectiveness of dicloxacillin sodium capsules and other antibacterial drugs, dicloxacillin sodium capsules should be used only to treat or prevent infections that are proven or strongly suspected to be caused by susceptible bacteria. When culture and susceptibility information are available, they should be considered in selecting or modifying antibacterial therapy. In the absence of such data, local epidemiology and susceptibility patterns may contribute to the empiric selection of therapy.

Dicloxacillin is indicated in the treatment of infections caused by penicillinase-producing staphylococci which have demonstrated susceptibility to the drug. Cultures and susceptibility tests should be performed initially to determine the causative organisms and their sensitivity to the drug (see CLINICAL PHARMACOLOGY – Susceptibility Testing) .

Dicloxacillin may be used to initiate therapy in suspected cases of resistant staphylococcal infections prior to the availability of laboratory test results. The penicillinase-resistant penicillins should not be used in infections caused by organisms susceptible to penicillin G. If the susceptibility tests indicate that the infection is due to an organism other than a resistant staphylococcus, therapy should not be continued with a penicillinase-resistant penicillin.

CONTRAINDICATIONS

Dicloxacillin sodium is contraindicated in persons who have shown hypersensitivity to any of the penicillins or any component of the formulations.

WARNINGS

Serious and occasionally fatal hypersensitivity (anaphylactic shock with collapse) reactions have occurred in patients receiving penicillin. The incidence of anaphylactic shock in all penicillin-treated patients is between 0.015% and 0.04%. Anaphylactic shock resulting in death has occurred in approximately 0.002% of the patients treated. Although anaphylaxis is more frequent following a parenteral administration, it has occurred in patients receiving oral penicillins.

When penicillin therapy is indicated, it should be initiated only after a comprehensive patient drug and allergy history has been obtained. If an allergic reaction occurs, dicloxacillin should be discontinued and appropriate therapy instituted. Individuals with a history of penicillin hypersensitivity may also experience allergic reactions when treated with a cephalosporin.

Clostridium difficile associated diarrhea (CDAD) has been reported with use of nearly all antibacterial agents, including dicloxacillin sodium, and may range in severity from mild diarrhea to fatal colitis. Treatment with antibacterial agents alters the normal flora of the colon leading to overgrowth of C. difficile.

C. difficile produces toxins A and B which contribute to the development of CDAD. Hypertoxin producing strains of C. difficile cause increased morbidity and mortality, as these infections can be refractory to antimicrobial therapy and may require colectomy. CDAD must be considered in all patients who present with diarrhea following antibiotic use. Careful medical history is necessary since CDAD has been reported to occur over two months after the administration of antibacterial agents.

If CDAD is suspected or confirmed, ongoing antibiotic use not directed against C. difficile may need to be discontinued. Appropriate fluid and electrolyte management, protein supplementation, antibiotic treatment of C. difficile, and surgical evaluation should be instituted as clinically indicated.

PRECAUTIONS

General

Prescribing dicloxacillin sodium capsules in the absence of a proven or strongly suspected bacterial infection or a prophylactic indication is unlikely to provide benefit to the patient and increases the risk of the development of drug-resistant bacteria.

Dicloxacillin should generally not be administered to patients with a history of sensitivity to any penicillin.

Penicillin should be used with caution in individuals with histories of significant allergies and/or asthma.
There is clinical and laboratory evidence of partial cross-allergenicity among penicillins and other β-lactam antibiotics including cephalosporins, cephamycins, and other 1-oxa-β-lactams. Whenever allergic reactions occur, penicillin should be withdrawn unless, in the opinion of the physician, the condition being treated is life-threatening and amenable only to penicillin therapy.

The oral route of administration should not be relied upon in patients with severe illness, or with nausea, vomiting, gastric dilatation, cardiospasm or intestinal hypermotility. Occasionally, patients will not absorb therapeutic amounts of orally administered penicillin.

Information for the Patient

Patients should be counselled that antibacterial drugs including dicloxacillin sodium capsules should only be used to treat bacterial infections. They do not treat viral infections (e.g., the common cold). When dicloxacillin sodium capsules are prescribed to treat a bacterial infection, patients should be told that although it is common to feel better early in the course of therapy, the medication should be taken exactly as directed. Skipping doses or not completing the full course of therapy may (1) decrease the effectiveness of the immediate treatment and (2) increase the likelihood that bacteria will develop resistance and will not be treatable by dicloxacillin sodium capsules or other antibacterial drugs in the future.

Diarrhea is a common problem caused by antibiotics which usually ends when the antibiotic is discontinued. Sometimes after starting treatment with antibiotics, patients can develop watery and bloody stools (with or without stomach cramps and fever) even as late as two or more months after having taken the last dose of the antibiotic. If this occurs, patients should contact their physician as soon as possible.

Patients receiving penicillins should be given the following information and instructions by the physician:

1. Patients should be told that penicillin is an antibacterial agent which will work with the body’s natural defenses to control certain types of infections. They should be told that the drug should not be taken if they have had an allergic reaction to any form of penicillin previously, and to inform the physician of any allergies or previous allergic reactions to any drugs they may have had (see WARNINGS).
2. Patients who have previously experienced an anaphylactic reaction to penicillin should be instructed to wear a medical identification tag or bracelet.
3. Because most antibacterial drugs taken by mouth are best absorbed on an empty stomach, patients should be directed, unless circumstances warrant otherwise, to take penicillin one hour before meals or two hours after eating (see CLINICAL PHARMACOLOGY - Pharmacokinetics).
4. Patients should be told to take the entire course of therapy prescribed, even if fever and other symptoms have stopped (see PRECAUTIONS - General).
5. If any of the following reactions occur, stop taking your prescription and notify the physician: shortness of breath, wheezing, skin rash, mouth irritation, black tongue, sore throat, nausea, vomiting, diarrhea, fever, swollen joints or any unusual bleeding or bruising (see ADVERSE REACTIONS).
6. Do not take any additional medications without physician approval, including nonprescription drugs such as antacids, laxatives or vitamins.

Laboratory Tests

Bacteriologic studies to determine the causative organisms and their susceptibility to the penicillinase-resistant penicillins should be performed (see CLINICAL PHARMACOLOGY - Microbiology). In the treatment of suspected staphylococcal infections, therapy should be changed to another active agent if culture tests fail to demonstrate the presence of staphylococci.

Periodic assessment of organ system function, including renal, hepatic and hematopoietic, should be made during prolonged therapy with the penicillinase-resistant penicillins.

Blood cultures, white blood cell and differential cell counts should be obtained prior to initiation of therapy and at least weekly during therapy with penicillinase-resistant penicillins.

Periodic urinalysis, blood urea nitrogen and creatinine determinations should be performed during therapy with the penicillinase-resistant penicillins and dosage alterations should be considered if these values become elevated. If any impairment of renal function is suspected or known to exist, a reduction in the total dosage should be considered and blood levels monitored to avoid possible neurotoxic reactions (see DOSAGE AND ADMINISTRATION).

AST (SGOT) and ALT (SGPT) values should be obtained periodically during therapy to monitor for possible liver function abnormalities.

Drug Interactions

Tetracycline, a bacteriostatic antibiotic, may antagonize the bactericidal effect of penicillin and concurrent use of these drugs should be avoided.

Probenecid administered concomitantly with penicillins increases and prolongs serum penicillin levels (see DOSAGE AND ADMINISTRATION).

Penicillinase-resistant penicillins, like other penicillins, are physically and/or chemically incompatible with aminoglycosides and can inactivate the drugs in vitro. In vitro mixing of penicillins and aminoglycosides should be avoided during concomitant therapy and the drugs should be administered separately. Penicillins can inactivate aminoglycosides in vitro in serum samples from patients receiving both drugs, which could produce falsely decreased results in serum aminoglycoside assays of the serum samples.

Dicloxacillin may reduce the anticoagulant response to dicumarol and warfarin. Careful monitoring of prothrombin times is suggested during concomitant therapy, and dosage of the anticoagulant should be adjusted as required. The mechanism of this possible interaction is unclear, but may be due to hepatic enzyme induction.

Carcinogenesis, Mutagenesis, Impairment of Fertility

No long-term animal studies have been conducted with these drugs.

Studies on reproduction (nafcillin) in rats and rabbits reveal no fetal or maternal abnormalities before conception and continuously through weaning (one generation).

Pregnancy

Reproduction studies performed in the mouse, rat and rabbit have revealed no evidence of impaired fertility or harm to the fetus due to the penicillinase-resistant penicillins. Human experience with the penicillins during pregnancy has not shown any positive evidence of adverse effects on the fetus. There are, however, no adequate or well-controlled studies in pregnant women showing conclusively that harmful effects of these drugs on the fetus can be excluded. Because animal reproduction studies are not always predictive of human response, this drug should be used during pregnancy only if clearly needed.

Nursing Mothers

Penicillins are excreted in breast milk. Caution should be exercised when penicillins are administered to a nursing woman.

Pediatric Use

Because of incompletely developed renal function in newborns, penicillinase-resistant penicillins (especially methicillin) may not be completely excreted, with abnormally high blood levels resulting. Frequent monitoring of blood levels is advisable in this group, with dosage adjustments when necessary. All newborns treated with penicillins should be monitored closely for clinical and laboratory evidence of toxic or adverse effects (see DOSAGE AND ADMINISTRATION). Experience in the neonatal period is limited. Therefore a dose for the newborn is not recommended.

Geriatric Use

Clinical studies of dicloxacillin sodium capsules did not include sufficient numbers of subjects aged 65 and over to determine whether they respond differently from younger subjects. Other reported clinical experience has not identified differences in responses between the elderly and younger patients. In general, dose selection for an elderly patient should be cautious, usually starting at the low end of the dosing range, reflecting the greater frequency of decreased hepatic, renal, or cardiac function, and of concomitant disease or other drug therapy.

Postmarketing Experience

Rare reports have been received during postmarketing surveillance of esophageal burning, esophagitis, and esophageal ulceration, particularly after ingestion of dicloxacillin capsules with an insufficient quantity of water and/or before going to bed. To minimize the risk of developing such events, dicloxacillin should be taken with at least 4 fluid ounces (120 mL) of water and dicloxacillin should NOT be taken in the supine position or immediately before going to bed.

ADVERSE REACTIONS

Hypersensitive Reactions

The reported incidence of allergic reactions to penicillin ranges from 0.7% to 10% (see WARNINGS). Sensitization is usually the result of treatment, but some individuals have had immediate reactions to penicillin when first treated. In such cases, it is thought that the patients may have had prior exposure to the drug via trace amounts present in milk and vaccines.

Two types of allergic reactions to penicillin are noted clinically, immediate and delayed.

Immediate reactions usually occur within 20 minutes of administration and range in severity from urticaria and pruritus to angioneurotic edema, laryngospasm, bronchospasm, hypotension, vascular collapse and death. Such immediate anaphylactic reactions are very rare (see WARNINGS) and usually occur after parenteral therapy, but have occurred in patients receiving oral therapy. Another type of immediate reaction, an accelerated reaction, may occur between 20 minutes and 48 hours after administration and may include urticaria, pruritus and fever. Although laryngeal edema, laryngospasm and hypotension occasionally occur, fatality is uncommon.

Delayed allergic reactions to penicillin therapy usually occur after 48 hours and sometimes as late as two to four weeks after initiation of therapy. Manifestations of this type of reaction include serum sickness-like symptoms (i.e., fever, malaise, urticaria, myalgia, arthralgia, abdominal pain) and various skin rashes.

Gastrointestinal Reactions

Nausea, vomiting, diarrhea, stomatitis, black or hairy tongue and other symptoms of gastrointestinal irritation may occur, especially during oral penicillin therapy.

Pseudomembranous colitis has been reported with the use of dicloxacillin. Therefore, it is important to consider its diagnosis in patients who develop diarrhea in association with dicloxacillin use.

Reports have been received during postmarketing surveillance of esophageal burning, esophagitis, and esophageal ulceration, particularly after ingestion of dicloxacillin capsules with an insufficient quantity of water and/or before going to bed (see PRECAUTIONS and DOSAGE AND ADMINISTRATION).

Nervous System Reactions

Neurotoxic reactions similar to those observed with penicillin G (e.g., lethargy, confusion, twitching, multifocal myoclonus, localized or generalized epileptiform seizures) may occur with large intravenous doses of the penicillinase-resistant penicillins, especially with patients with renal insufficiency.

Renal Reactions

Renal tubular damage and interstitial nephritis have been associated with the administration of methicillin sodium and, infrequently, with the administration of nafcillin and oxacillin. Manifestations of this reaction may include rash, fever, eosinophilia, hematuria, proteinuria and renal insufficiency. Methicillin-induced nephropathy does not appear to be dose-related and is generally reversible upon prompt discontinuation of therapy.

Hematologic Reactions

Eosinophilia, hemolytic anemia, agranulocytosis, neutropenia, leukopenia, granulocytopenia, thrombocytopenia, and bone marrow depression have been associated with the use of penicillinase-resistant penicillins.

Hepatic Reactions

Hepatotoxicity, characterized by fever, nausea and vomiting associated with abnormal liver function tests, mainly elevated AST (SGOT) levels, has been associated with the use of oxacillin and cloxacillin. Chloestatic hepatitis has been reported rarely. Asymptomatic, transient increases in serum concentrations of alkaline phosphatase, AST (SGOT), and ALT (SGPT) have been reported.

DOSAGE AND ADMINISTRATION

Concurrent administration of the penicillinase-resistant penicillins and probenecid increases and prolongs serum penicillin levels.

Probenecid decreases the apparent volume of distribution and slows the rate of excretion by competitively inhibiting renal tubular secretion of penicillin. Penicillin-probenecid therapy is generally limited to those infections where very high serum levels of penicillin are necessary.

Oral preparations of the penicillinase-resistant penicillins should not be used as initial therapy in serious, life-threatening infections (see PRECAUTIONS - General). Oral therapy with the penicillinase-resistant penicillins may be used to follow up the previous use of a parenteral agent as soon as the clinical condition warrants.

RECOMMENDED DOSAGES FOR DICLOXACILLIN SODIUM IN MILD TO MODERATE AND SEVERE INFECTIONS
DRUG | ADULTS |  | CHILDREN
 | Mild to Moderate | Severe | Mild to Moderate | Severe
Dicloxacillin | 125 mg every; 6 hours | 250 mg every; 6 hours | 12.5 mg/kg/day ^1 in equally divided doses every 6 hours | 25 mg/kg/day ^1 in equally divided doses every 6 hours

^1. Patients weighing less than 40 kg (88 lbs)

Dicloxacillin is best absorbed when taken on an empty stomach, and should be administered at least 1 hour before or 2 hours after meals. Dicloxacillin should be taken with at least 4 fluid ounces (120 mL) of water and should not be taken in the supine position or immediately before going to bed (see PRECAUTIONS).

HOW SUPPLIED

Dicloxacillin Sodium Capsules USP are available as follows:

250 mg: Each capsule contains dicloxacillin sodium monohydrate equivalent to 250 mg dicloxacillin (anhydrous), with green colored cap and light green colored body, imprinted "TEVA" on the cap and “3123” on the body, available in:

NDC 55289-592-10 Bottles of 10 capsules

NDC 55289-592-20 Bottles of 20 capsules

NDC 55289-592-28 Bottles of 28 capsules

NDC 55289-592-40 Bottles of 40 capsules

Store at 20° to 25°C (68° to 77°F) [See USP Controlled Room Temperature].

Dispense in a tight, light-resistant container as defined in the USP, with a child-resistant closure (as required).

KEEP THIS AND ALL MEDICATIONS OUT OF THE REACH OF CHILDREN.

Package/Label Display Panel

Dicloxacillin
Sodium
Capsules USP
250 mg*